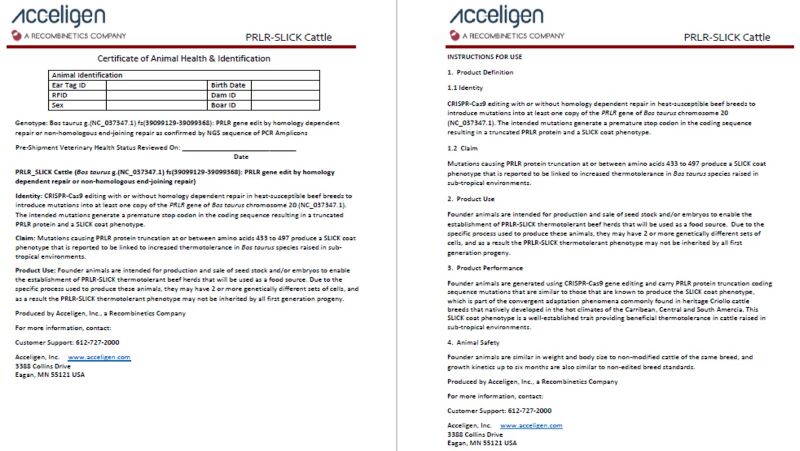 DRUG LABEL: PRLR-SLICK Cattle
NDC: 86086-006 | Form: NOT APPLICABLE
Manufacturer: Recombinetics, Inc.
Category: other | Type: INTENTIONAL ANIMAL GENOMIC ALTERATION LABEL
Date: 20240724

ACTIVE INGREDIENTS: SLICK ALTERATION DISRUPTING BOS TAURUS G.(NC_037347.1) FS(39099129-39099368) IN EXON 9 OF PRLR GENE IN BOS TAURUS 1 [arb'U]/1 [arb'U]

PRLR-SLICK Cattle

STATEMENT OF IDENTITY

Identity: CRISPR-Cas9 editing with or without homology dependent repair in heat-susceptible beef breeds to introduce mutations into at least one copy of the PRLR gene of Bos taurus chromosome 20 (NC_037347.1). The intended mutations generate a premature stop codon in the coding sequence resulting in a truncated PRLR protein and a SLICK coat phenotype.

HEALTH CLAIM

Claim: Mutations causing PRLR protein truncation at or between amino acids 433 to 497 produce a SLICK coat phenotype that is reported to be linked to increased thermotolerance in Bos taurus species raised in sub-tropical environments.

INDICATIONS AND USAGE

Product Use: Founder animals are intended for production and sale of seed stock and/or embryos to enable the establishment of PRLR-SLICK thermotolerant beef herds that will be used as a food source. Due to the specific process used to produce these animals, they may have 2 or more genetically different sets of cells, and as a result the PRLR-SLICK thermotolerant phenotype may not be inherited by all first generation progeny.